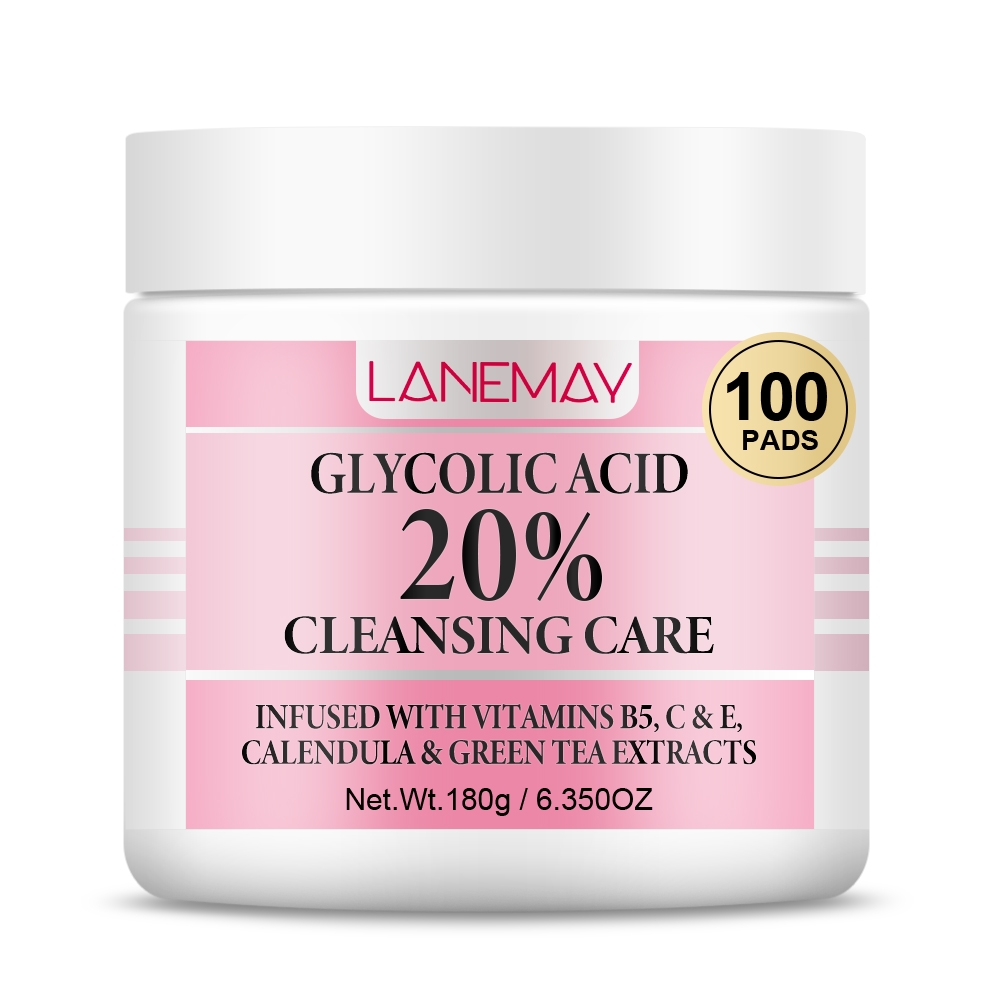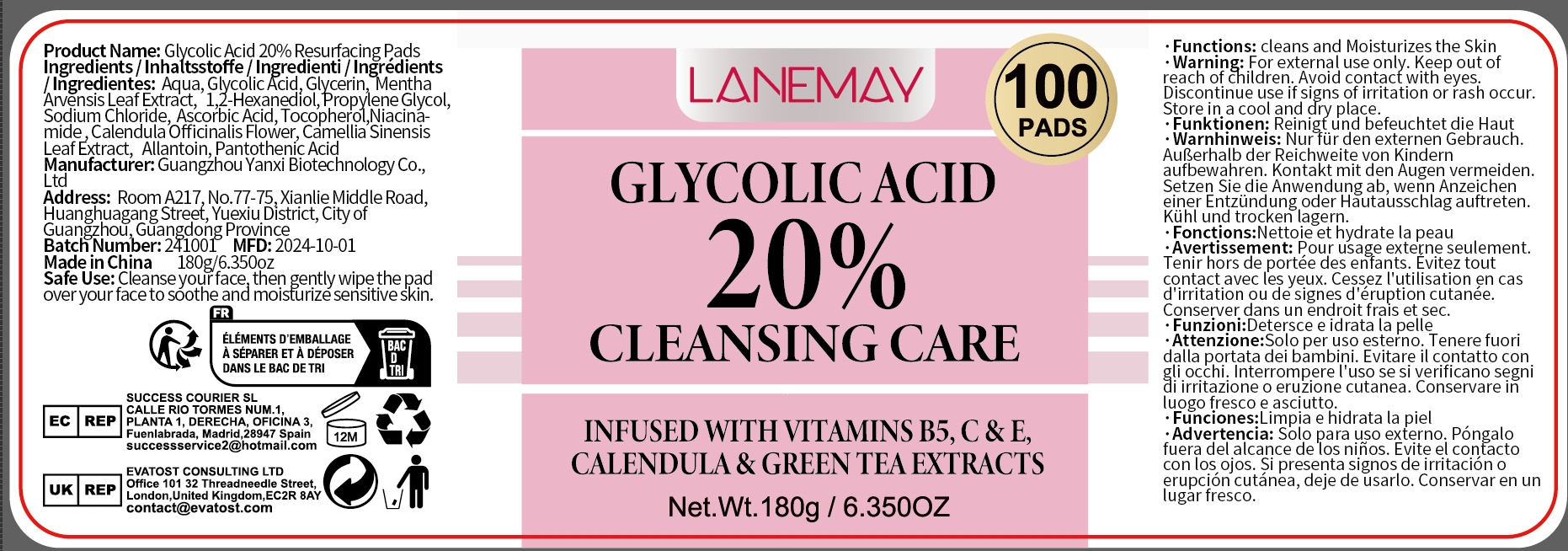 DRUG LABEL: Cleansing Care Pads
NDC: 84025-283 | Form: LIQUID
Manufacturer: Guangzhou Yanxi Biotechnology Co., Ltd
Category: otc | Type: HUMAN OTC DRUG LABEL
Date: 20241219

ACTIVE INGREDIENTS: GLYCERIN 8 mg/180 g; GLYCOLIC ACID 6 mg/180 g
INACTIVE INGREDIENTS: WATER

DOSAGE AND ADMINISTRATION

Cleanse your face,then gently wipe the pad over your face to soothe and moisturize sensitive skin.

WARNINGS

Keep out of children

INACTIVE INGREDIENT

Aqua

INDICATIONS AND USAGE

For daily skin care

Keep out of children

PURPOSE

Cleans and moisturizes the skin